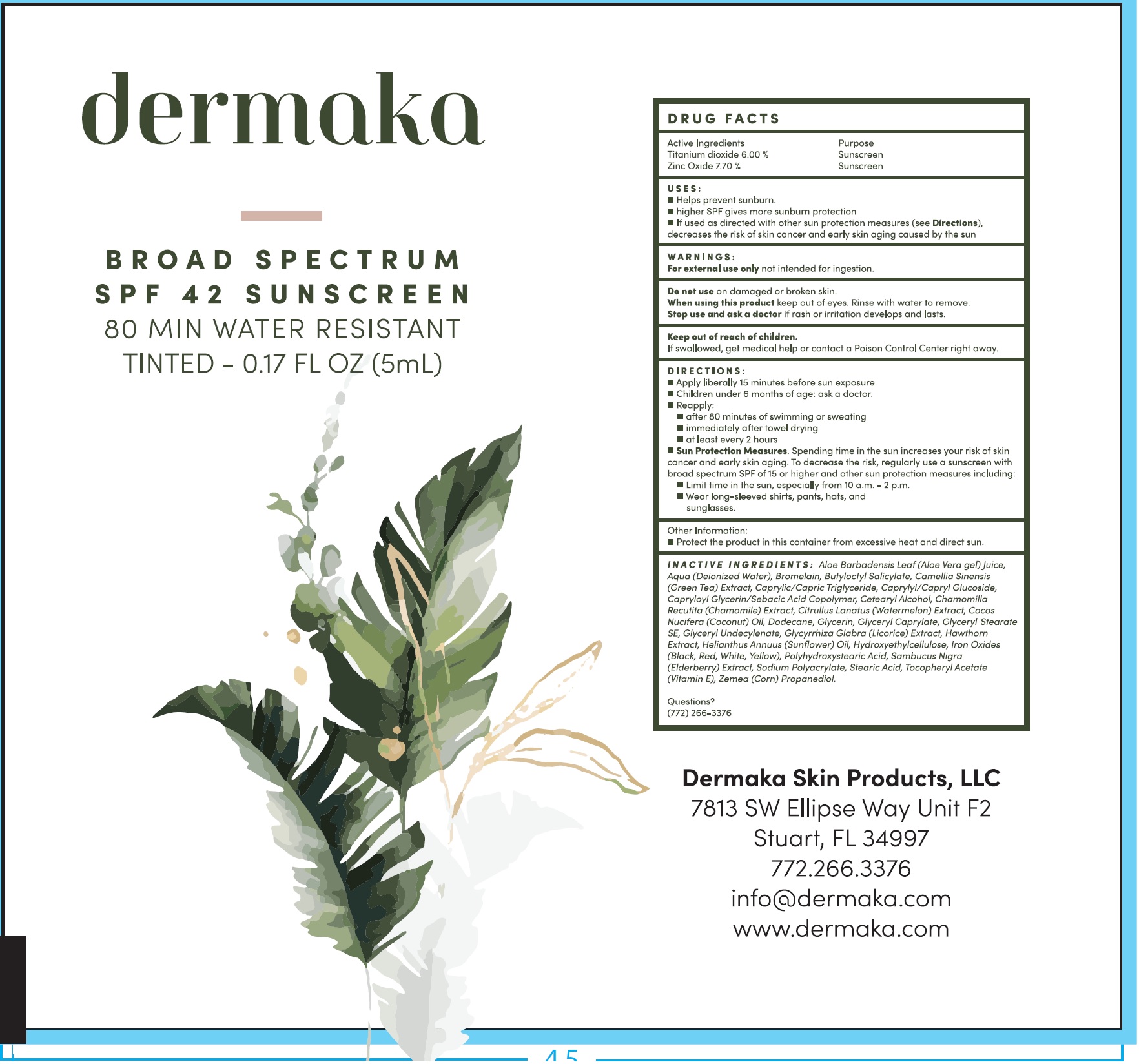 DRUG LABEL: Dermaka Sunscreen SPF 42, Tinted
NDC: 82240-619 | Form: CREAM
Manufacturer: DERMAKA SKIN PRODUCTS
Category: otc | Type: HUMAN OTC DRUG LABEL
Date: 20250616

ACTIVE INGREDIENTS: TITANIUM DIOXIDE 60 mg/1 mL; ZINC OXIDE 77 mg/1 mL
INACTIVE INGREDIENTS: ALOE VERA LEAF JUICE; WATER; BROMELAIN; BUTYLOCTYL SALICYLATE; GREEN TEA LEAF; MEDIUM-CHAIN TRIGLYCERIDES; CAPRYLYL/CAPRYL OLIGOGLUCOSIDE; CETOSTEARYL ALCOHOL; COCONUT OIL; DODECANE; GLYCERIN; GLYCERYL MONOCAPRYLATE; GLYCERYL STEARATE SE; HELIANTHUS ANNUUS FLOWERING TOP; HYDROXYETHYL CELLULOSE, UNSPECIFIED; FERRIC OXIDE RED; STEARIC ACID; .ALPHA.-TOCOPHEROL ACETATE; CORN

Dermaka Sunscreen SPF 42, Tinted

Active Ingredients

Titanium Dioxide 6.00 %
Zinc Oxide 7.70 %

Purpose

Sunscreen

USES:

- Helps prevent sunburn.
- higher SPF gives more sunburn protection
- If used as directed with other sun protection measures (see Directions), decreases the risk of skin cancer and early skin aging caused by the sun

WARNINGS:

For external use onlynot intended for ingestion.

Do not use

on damaged or broken skin.

When using this product

keep out of eyes. Rinse with water to remove.

Stop use and ask a doctor if

rash or irritation develops and lasts.

Keep out of reach of children.

If swallowed, get medical help or contact a Poison Control Center right away.

DIRECTIONS:

- Apply liberally 15 minutes before sun exposure.
- Children under 6 months of age: ask a doctor.
- Reapply:
- after 80 minutes of swimming or sweating
- immediately after towel drying
- at least every 2 hours
- Sun Protection Measures.Spending time in the sun increases your risk of skin cancer and early skin aging. To decrease the risk, regularly use a sunscreen with broad spectrum SPF of 15 or higher and other sun protection measures including:
- Limit time in the sun, especially from 10 a.m. - 2 p.m.
- Wear long-sleeved shirts, pants, hats, and sunglasses.

Other Information:

- Protect the product in this container from excessive heat and direct sun.

INACTIVE INGREDIENTS:

Aloe Barbadensis Leaf (Aloe Vera gel) Juice, Aqua (Deionized Water), Bromelain, Butyloctyl Salicylate, Camellia Sinensis (Green Tea) Extract, Caprylic/Capric Triglyceride, Caprylyl/Capryl Glucoside, Caprylyl Glycerin/Sebacic Acid Copolymer, Cetearyl Alcohol, Chamomilla Recutita (Chamomile) Extract, Citrullus Lanatus (Watermelon) Extract, Cocos Nucifera (Coconut) Oil, Dodecane, Glycerin, Glyceryl Caprylate, Glyceryl Stearate SE, Glyceryl Undecylenate, Glycyrrhiza Glabra (Licorice) Extract, Hawthorn Extract, Helianthus Annuus (Sunflower) Oil, Hydroxyethylcellulose, Iron Oxides (Black, Red, White, Yellow), Polyhydroxystearic Acid, Sambucus Nigra (Elderberry) Extract, Sodium Polyacrylate, Stearic Acid, Tocopheryl Acetate (Vitamin E), Zemea (Corn) Propanediol.

Questions?

(772) 266-3376